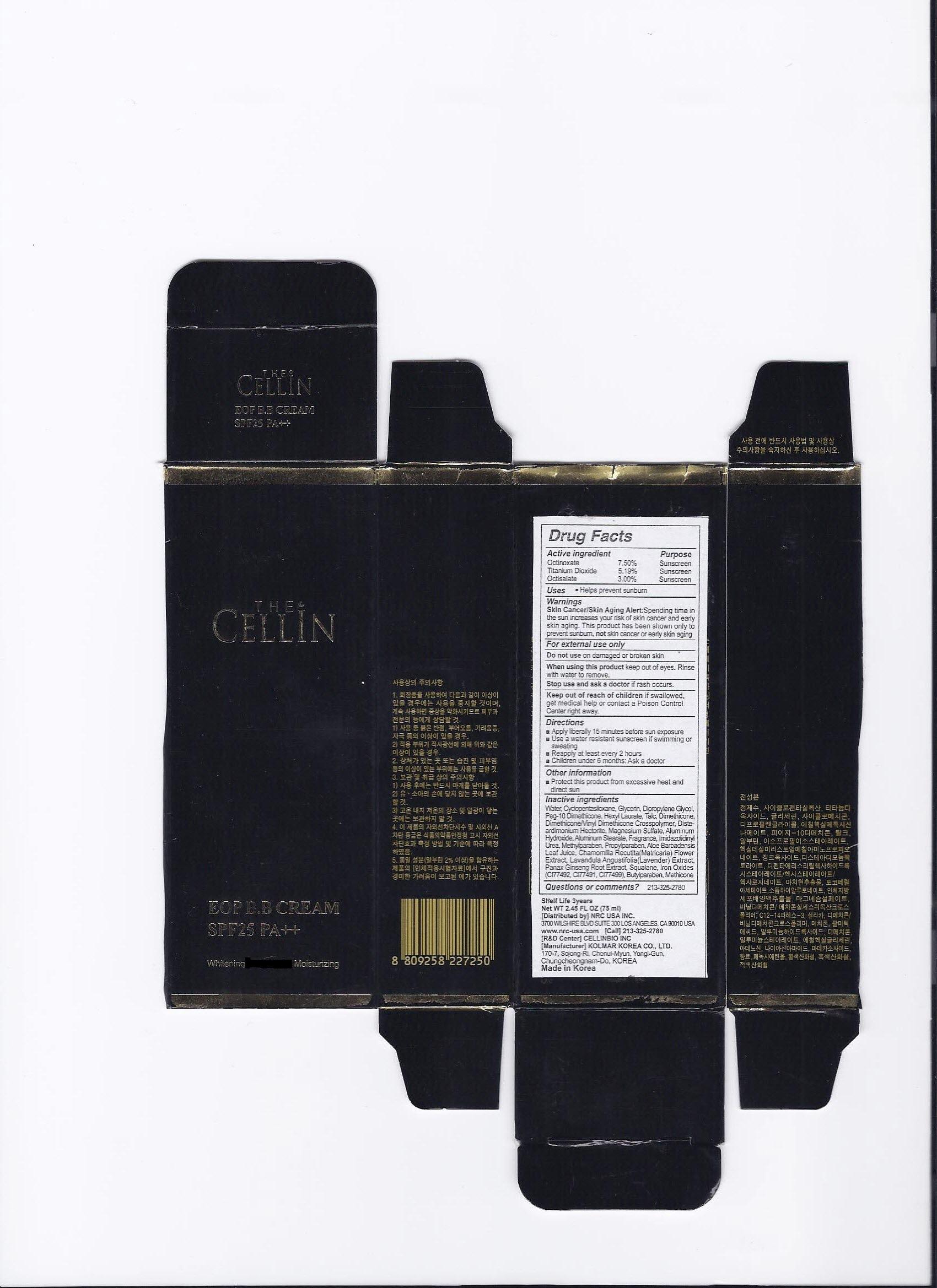 DRUG LABEL: The Cellin EOP B.B Cream
NDC: 76173-1004 | Form: EMULSION
Manufacturer: Cellinbio Co Ltd
Category: otc | Type: HUMAN OTC DRUG LABEL
Date: 20110727

ACTIVE INGREDIENTS: TITANIUM DIOXIDE 2.556 mL/40 mL; OCTINOXATE 1.2 mL/40 mL; ZINC OXIDE 0.768 mL/40 mL
INACTIVE INGREDIENTS: WATER; CYCLOMETHICONE 5; GLYCERIN; CYCLOMETHICONE; DIPROPYLENE GLYCOL; TALC; ARBUTIN; DISTEARYLDIMONIUM CHLORIDE; MAGNESIUM SULFATE, UNSPECIFIED; FERRIC OXIDE YELLOW; PORTULACA OLERACEA WHOLE; SILICON DIOXIDE; PHENOXYETHANOL; FERROSOFERRIC OXIDE; PALMITIC ACID; FERRIC OXIDE RED; ALUMINUM HYDROXIDE; DIMETHICONE; ALUMINUM STEARATE; ETHYLHEXYLGLYCERIN; .ALPHA.-TOCOPHEROL ACETATE, D-; HYALURONATE SODIUM; ADENOSINE; NIACINAMIDE

The Cellin EOP B.B Cream

Drug Facts

Active ingredient
Titanium Dioxide 6.39%
Ethylhexyl Methoxycinnamate 3.00%
Zinc Oxide 1.92%

Purpose

Sunscreen

Keep out of reach of children if swallowed, get medical help or contact a Poison Control Center right away.

Indication & Usage

Directions
After finishing your basic skincare, apply an appropriate amount of this cream all around the face
Apply liberally 15 minutes before sun exposure
Use a water resistant sunscreen if swimming or sweating
Reapply at least every 2 hours(when used as sunscreen)
Children under 6 months: Ask a doctor

Warnings

Skin Cancer/Skin Aging Alert: Spending time in the sun increases your risk of skin cancer and early skin aging. This product has been shown only to prevent sunburn, not skin cancer or early skin aging
For extenal use only
Do not use on damaged or broken skin. If sun irritation develops or increases.
When using this product keep out of eyes. Rinse with water to remove.
Stop use and ask a doctor if rash or irritation develops and lasts

Dosage & Administration

Uses
Helps prevent sunburn
Foundation Effect
Moisturizing
Skin Smoothing

Inactive Ingredient

Water, Cyclopentasiloxane, Glycerin, Cyclomethicone, Dipropylene Glycol, Peg-10 Dimethicone, Talc, Arbutin, Hexyldecyl Myristoyl Methylaminopropionate, Isopropyl Isostearate, Dipentaerythrityl Hexahydroxystearate/Hexastearate/Hexarosinate, Disteardimonium Hectorite, Magnesium Sulfate, Iron Oxides(CI 77492), Vinyl Dimethicone/Methicone Silsesquioxane Crosspolymer, C12-14 Pareth-3, Portulaca Oleracea Extract, Silica, Dimethicone/Vinyl Dimethicone crosspolymer, Phenoxyethanol, Methicone, Iron Oxides(CI 77499), Palmitic Acid, Iron Oxides(CI 77491), Aluminum Hydroxide, Dimethicone, Aluminum Stearate, Ethylhexylglycerin, Fragrance, Tocopheryl Acetate, Sodium Hyaluronate, Human Adipocyte Conditioned Media Extract, Adenosine, Madecassoside, Niacinamide

The Cellin EOP B.B Cream

NRC The Cellin EOP B.B Cream

Net WT.1.35(40ml)